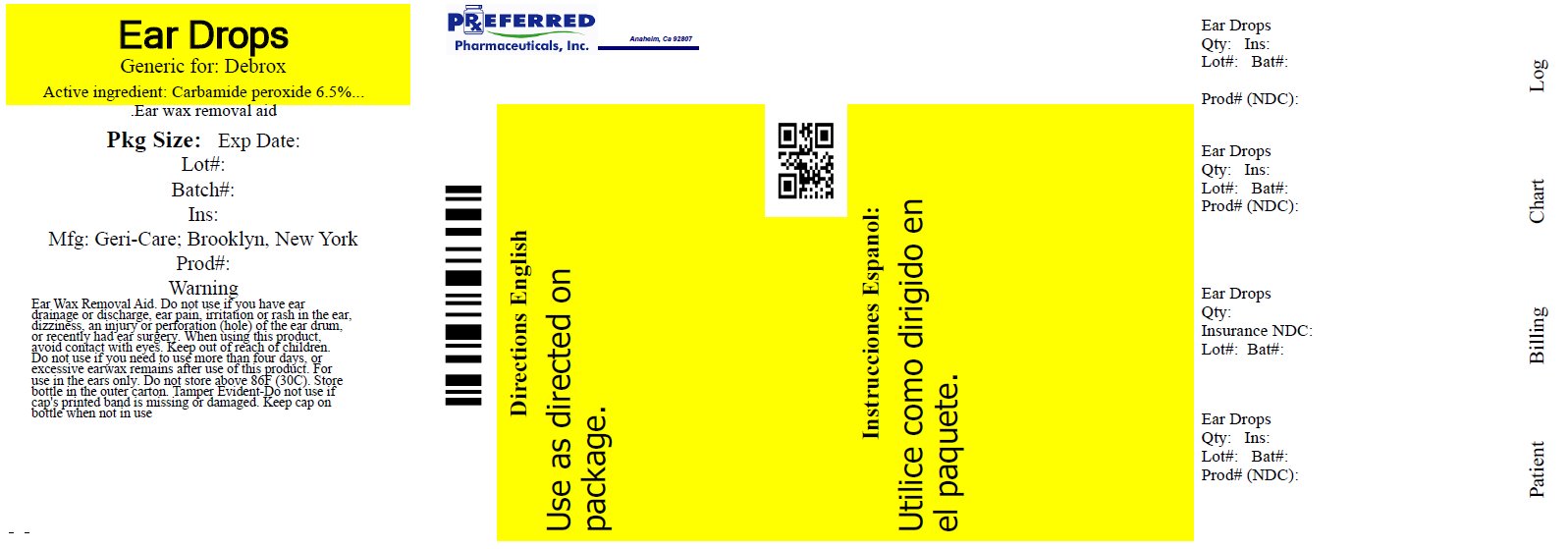 DRUG LABEL: Ear Wax Removal Drops
NDC: 68788-7498 | Form: SOLUTION/ DROPS
Manufacturer: Preferred Pharmaceuticals, Inc.
Category: otc | Type: HUMAN OTC DRUG LABEL
Date: 20200302

ACTIVE INGREDIENTS: CARBAMIDE PEROXIDE 65 mg/1 mL
INACTIVE INGREDIENTS: GLYCERIN; ANHYDROUS CITRIC ACID; PROPYLENE GLYCOL; SODIUM CITRATE, UNSPECIFIED FORM; SODIUM LAURYL SULFATE; TARTARIC ACID

Drug Facts

Active ingredient

Carbamide Peroxide, 6.5%

PURPOSE

Earwax removal aid

Uses

For occasional use as an aid to soften, loosen and remove excessive ear wax.

Warnings

Do not use if you have

- eardrainage, discharge, ear pain,irritation
- rashin the ear,or are dizzy
- injuryor perforation (hole) of the ear drum or after ear surgery

When using this product

- do not use for more than four days
- avoid contact with the eyes. If accidental contact with the eyes occurs, flush eyes with water and consult a doctor
- if excessive earwax remains after the use of this product, consult a doctor

Keep out of the reach of children

If swallowed, get medical help or contact a Poison Control Center right away.

Directions FOR USE IN THE EAR ONLY

- Adults and children over 12 years of age:
- Tilt head sideways and place 5 to 10 drops into ear.
- Tip of applicator should not enter ear canal.
- Keep drops in ear for several minutes by keeping head tilted or placing cotton in the ear.
- Use twice daily for up to 4 days if needed, or as directed by a doctor.
- Any earwax remaining after treatment may be removed by gently flushing the ear with warm water, using a soft rubber bulb ear syringe.
- When the ear canal is irrigated, the tip of the ear syringe should not obstruct the flow of water leaving the ear canal.
- Children under 12 years: consult a doctor.

Other information

- Protect from heat and direct sunlight
- Keep cap on bottle when not in use.
- Lot No. and EXP date: see label, bottom container or box.
NDC 68788-7496-01 1 Bottle .5FL OZ

Relabeled by Preferred Pharmaceuticals, Inc.

Inactive ingredients

Citric Acid, Glycerin, Propylene Glycol, Sodium Citrate, Sodium Lauryl Sulfate, Tartaric Acid

Principal Display Panel Bottle Label 0.5 FL OZ

Preferred Plus Pharmacy

Ear Wax Removal drops

Carbamide Peroxide 6.5%

0.5 FL OZ (15ml)

NDC: 68788-7498-01 Bottle .5 FL OZ

Relabeled by Preferred Pharmaceuticals, Inc.